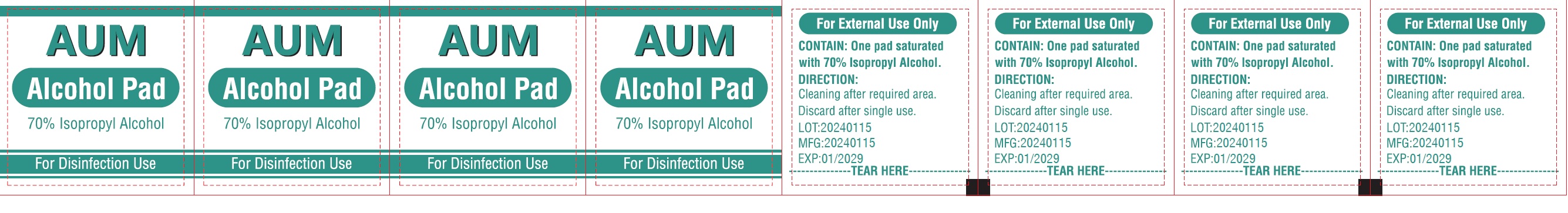 DRUG LABEL: AUM Alcohol Pad
NDC: 73317-8801 | Form: SWAB
Manufacturer: SLV PHARMACEUTICALS LLC DBA AUM PHARMACEUTICALS
Category: otc | Type: HUMAN OTC DRUG LABEL
Date: 20250226

ACTIVE INGREDIENTS: ISOPROPYL ALCOHOL 0.7 mL/1 1
INACTIVE INGREDIENTS: WATER

AUM Alcohol Pads
70 percent Isopropyl Alcohol

Active Ingredient

Isopropyl Alcohol, 70% v/v

Purpose

Antiseptic, Sterile Solution

Uses

Antiseptic cleanser

Kills harmful bacteria and germs

First aid to help prevent infection

Warnings

For External Use Only

Avoid contact with the eyes

If contact occurs, flush eyes with water

Do Not Use

With electrocautery prodedures

In the eyes

Stop Use and ask a doctor if

Irritation and redness develops

If condition persists for more than 72 hours, consult a physician

Discontinue use and consult a healthcare practitioner if

Irritation develops

Keep out of reach of children

If swallowed, get medical help or contact a Poison Control Center right away

Directions

Cleaning after required area

Discard after single use

Other Information

Store at room temperature 15°-30°C (59°-86°F)

Avoid excessive heat

Inactive Ingredients

Water